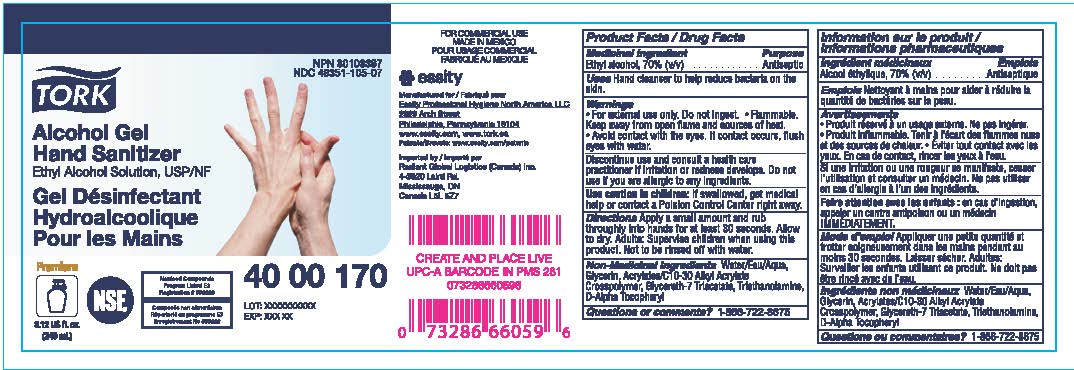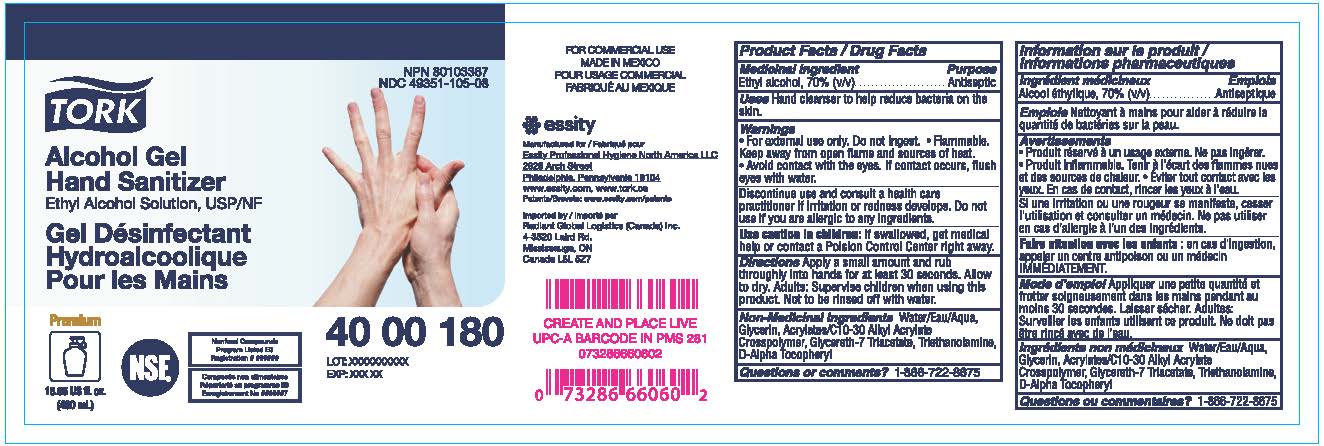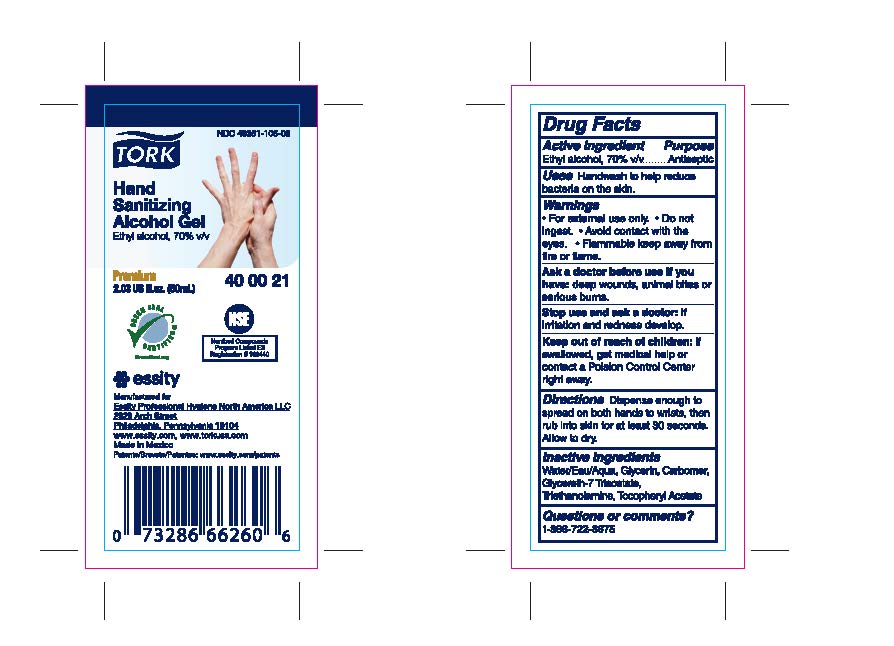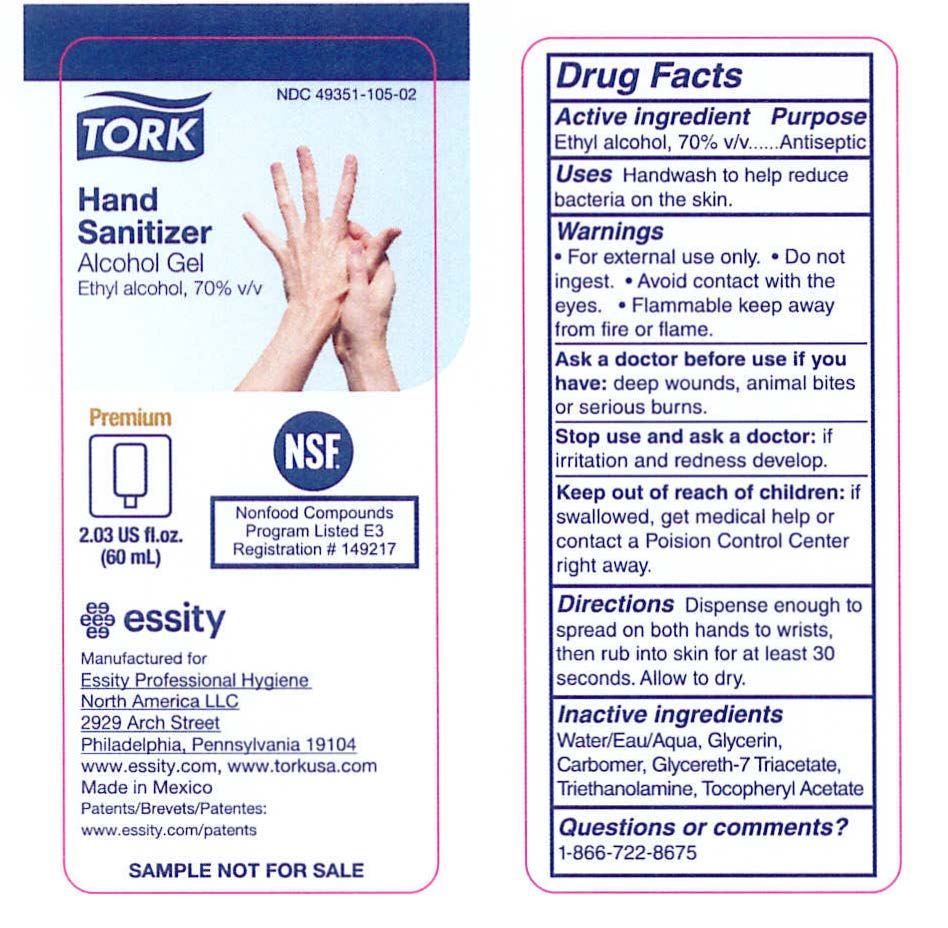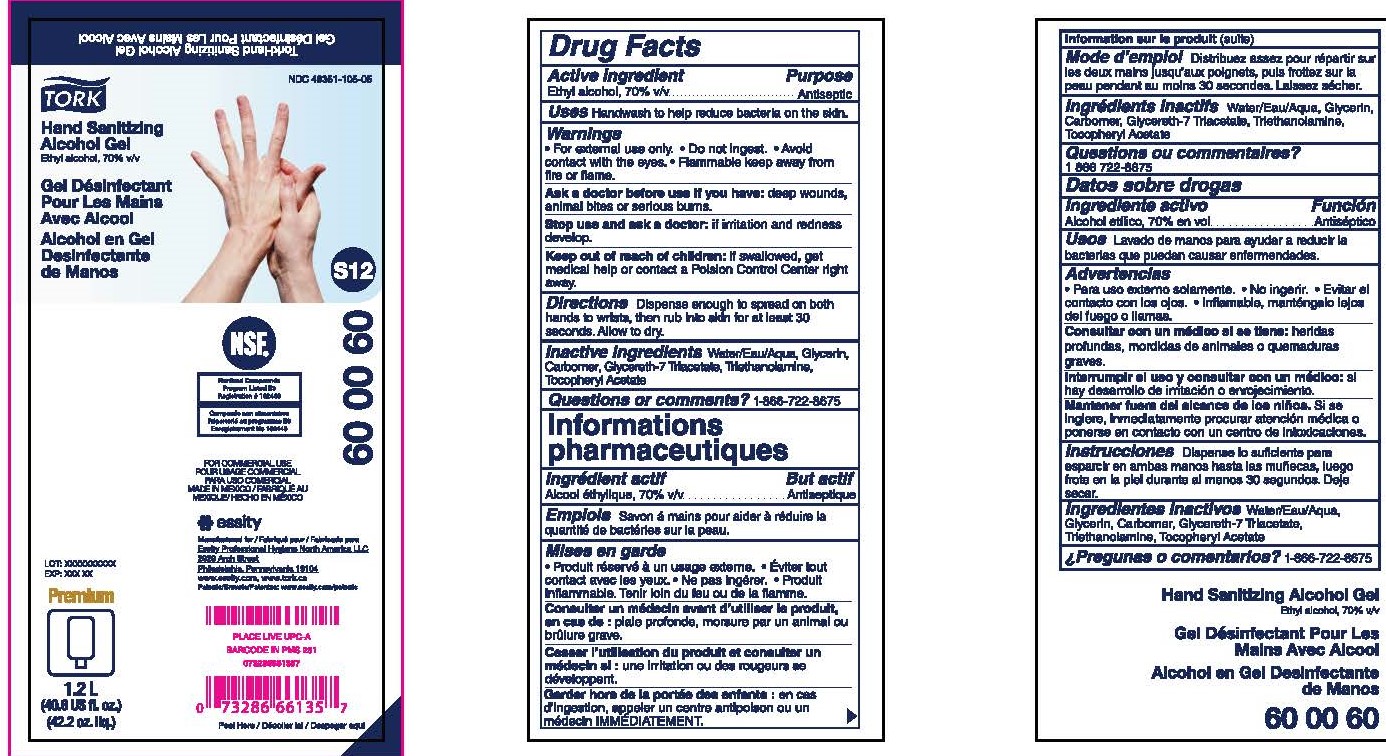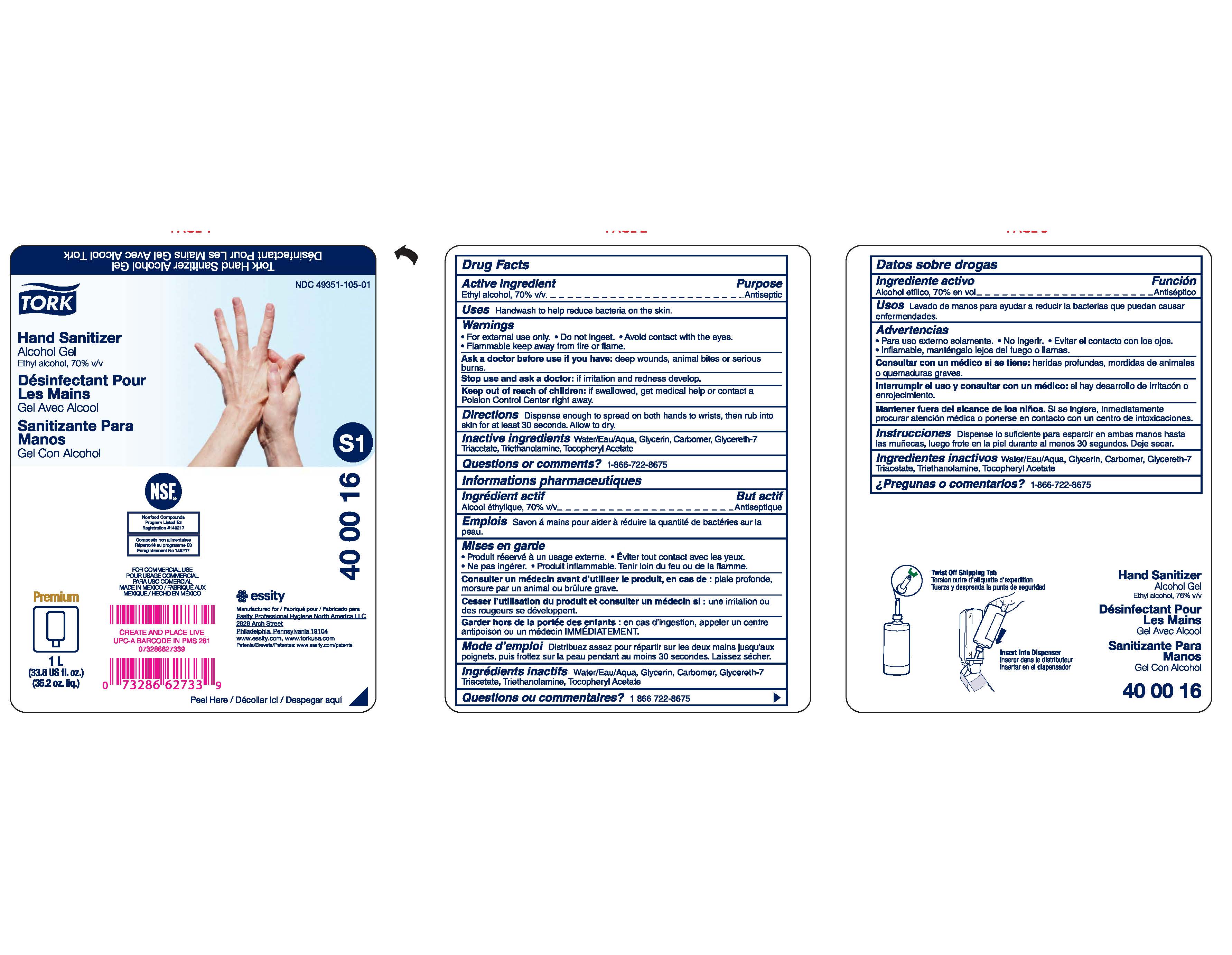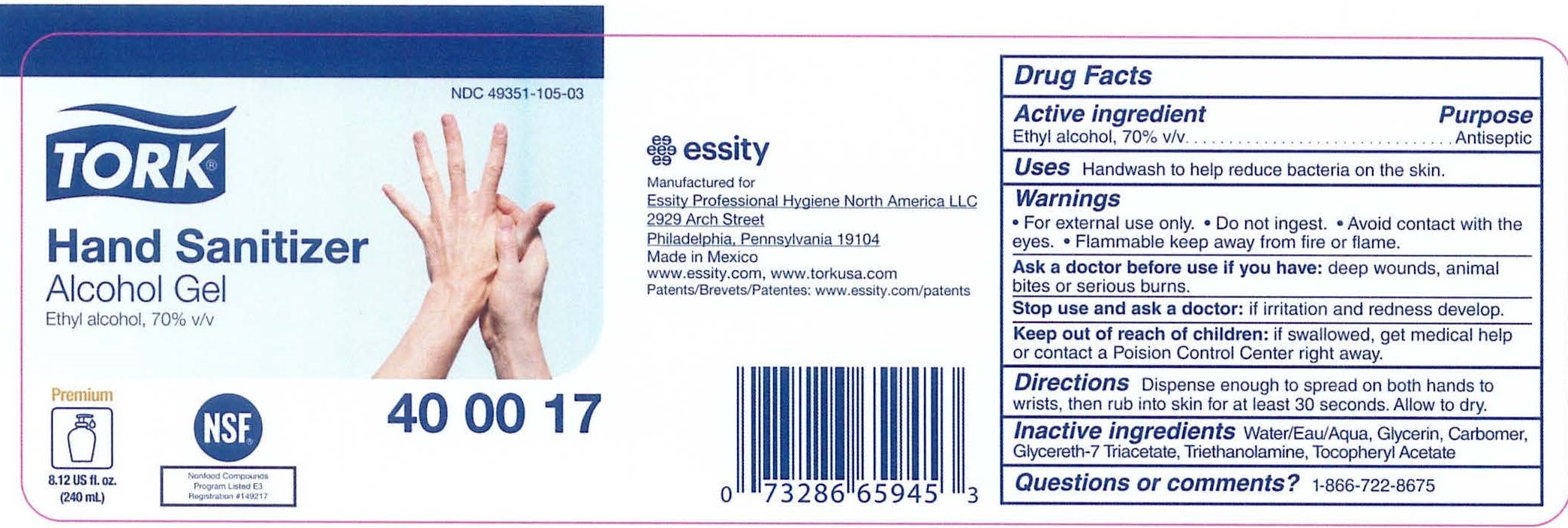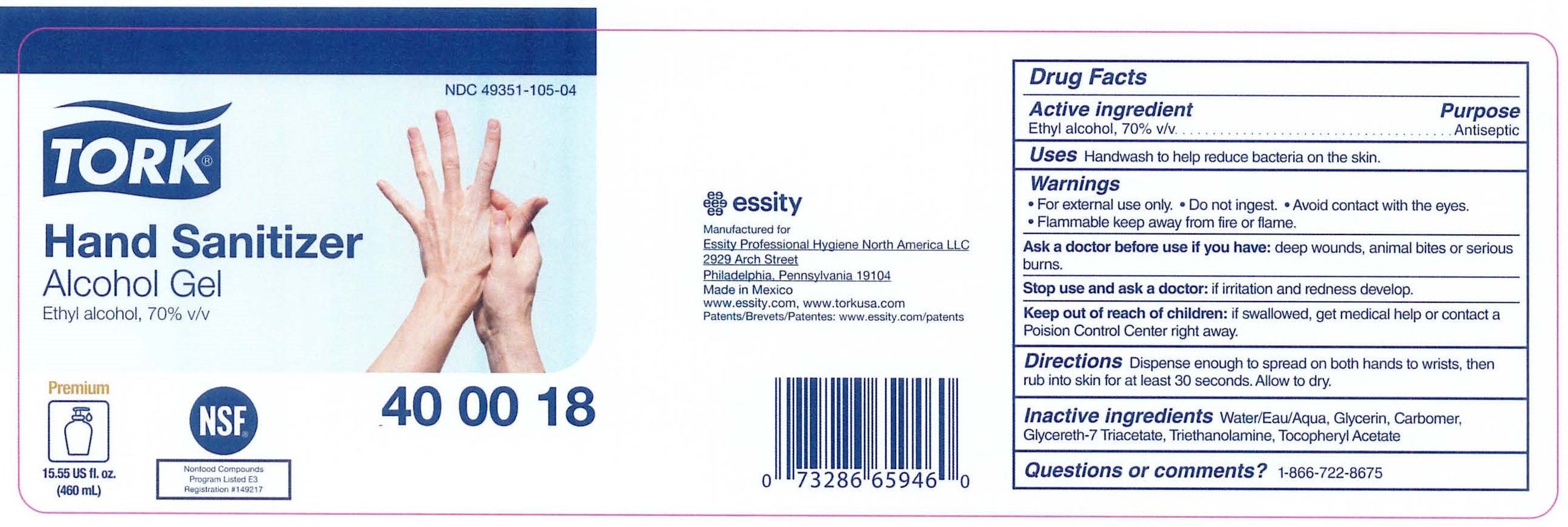 DRUG LABEL: Tork Hand Sanitizer Alcohol Gel
NDC: 49351-105 | Form: GEL
Manufacturer: Essity Professional Hygiene North America LLC
Category: otc | Type: HUMAN OTC DRUG LABEL
Date: 20240502

ACTIVE INGREDIENTS: ALCOHOL 70 mL/100 mL
INACTIVE INGREDIENTS: GLYCERETH-7 TRIACETATE; WATER; TROLAMINE; GLYCERIN; CARBOMER INTERPOLYMER TYPE A (ALLYL SUCROSE CROSSLINKED); .ALPHA.-TOCOPHEROL, D-

49351-105

Drug Facts

Active ingredient

Ethyl Alcohol, 70% v/v

Purpose

Antiseptic

Uses

Handwash to help reduce bacteria on the skin.

Warnings

- For external use only.
- Do not ingest.
- Avoid contact with the eyes.
- Flammable keep away from fire or flame.

Ask a doctor before use if you have:

deep wounds, animal bites or serious burns.

Stop use and ask a doctor if

irritation and redness develop.

Keep out of reach of children.

If swallowed, get medical help or contact a Poison Control Center right away.

Directions

Dispense enough to spread on both hands to wrists, then rub into skin for at least 30 seconds. Allow to dry.

Inactive ingredients

Water/Eau/Aqua, Glycerin, Carbomer, Glycereth-7 Triacetate, Triethanolamine, Tocopheryl Acetate

Questions or Comments?

1-866-722-8675

PACKAGE LABEL

TORK®

Hand Sanitizer

Alcohol Gel

Ethyl Alcohol, 70% v/v

NDC 49351-105-01

Manufactured for Essity Professional Hygiene North America, LLC

2929 Arch Street

Philadelphia, PA 19104

www.essity.com, www.torkusa.com

Made in Mexico

Premium